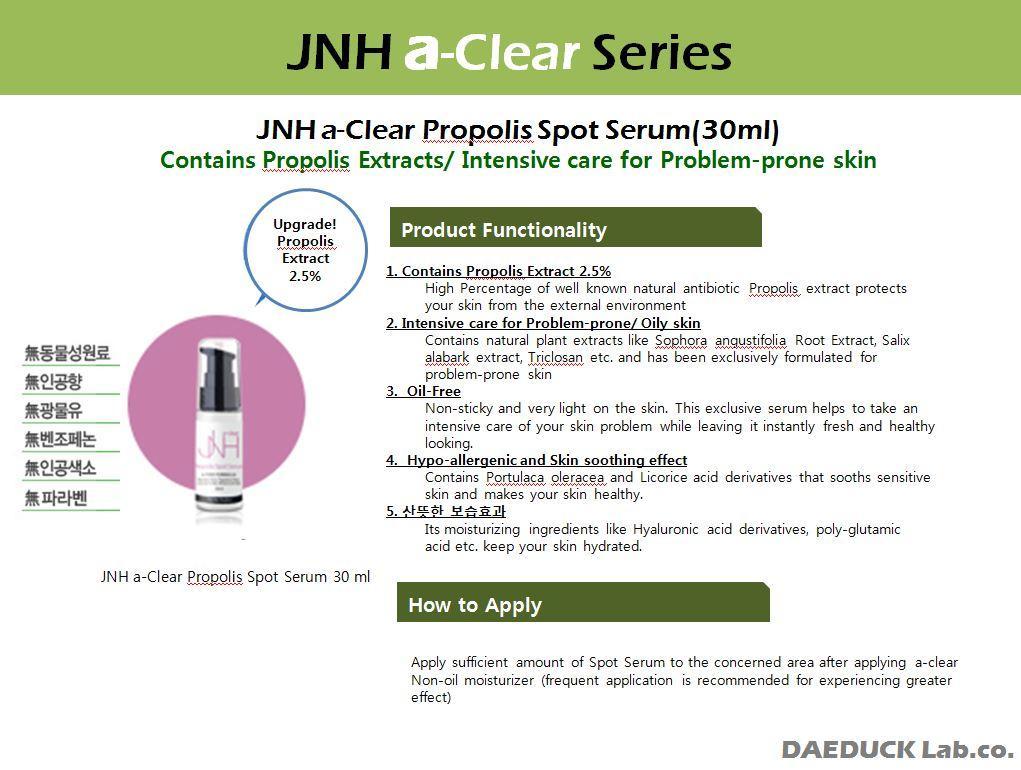 DRUG LABEL: JNH a-Clear Propolis Spot Serum
NDC: 53010-5001 | Form: LIQUID
Manufacturer: Daeduck Lab Co., Ltd.
Category: otc | Type: HUMAN OTC DRUG LABEL
Date: 20141015

ACTIVE INGREDIENTS: GLYCERIN 2 g/100 mL
INACTIVE INGREDIENTS: AZELAIC ACID; HYALURONATE SODIUM

Drug Facts

ACTIVE INGREDIENT

glycerin

INACTIVE INGREDIENT

triethanolamine, azelaic acid, portulaca oleracea ext, propolis ext, sodium hyaluronate, polyglutamic acid

PURPOSE

skin protectant

keep out or reach of the children

INDICATIONS AND USAGE

apply appropriate to skin

WARNINGS

- avoid direct sun exposure, keep it refrigerated or in cooler places
- avoid contact with eye

DOSAGE AND ADMINISTRATION

for exernal use only